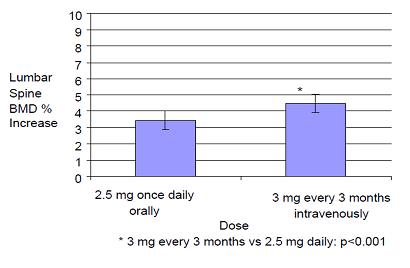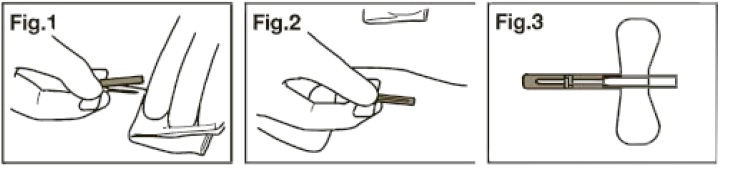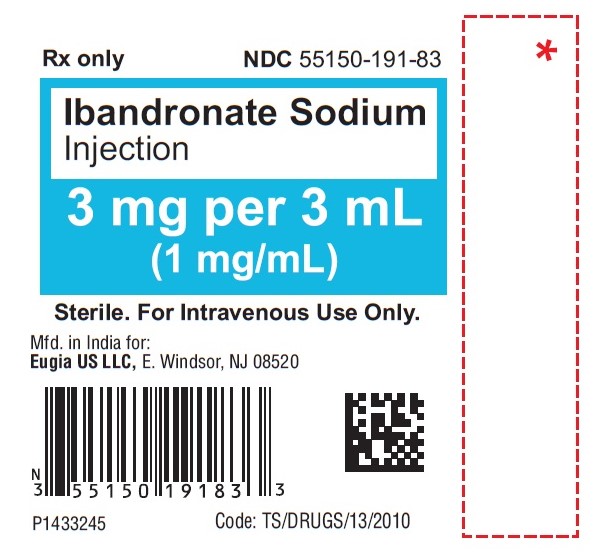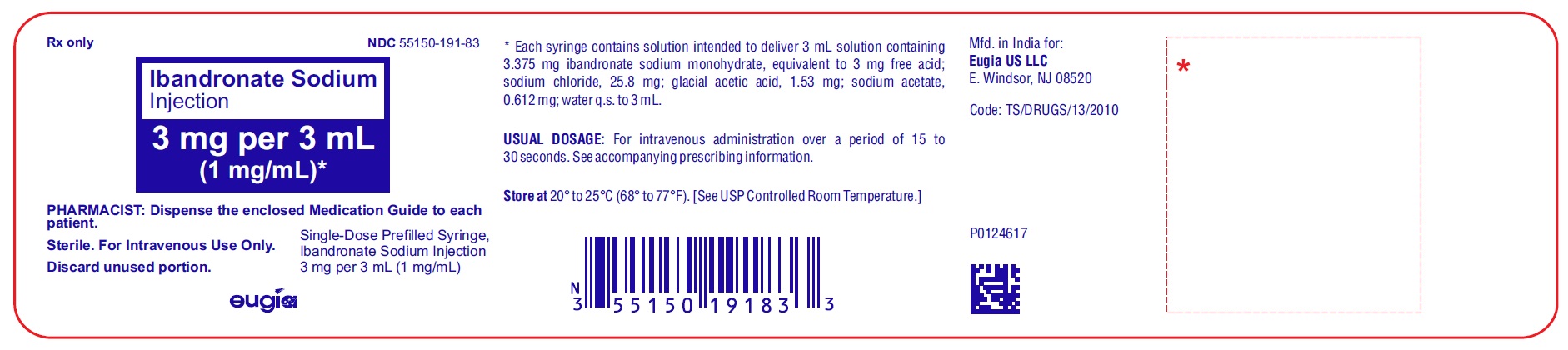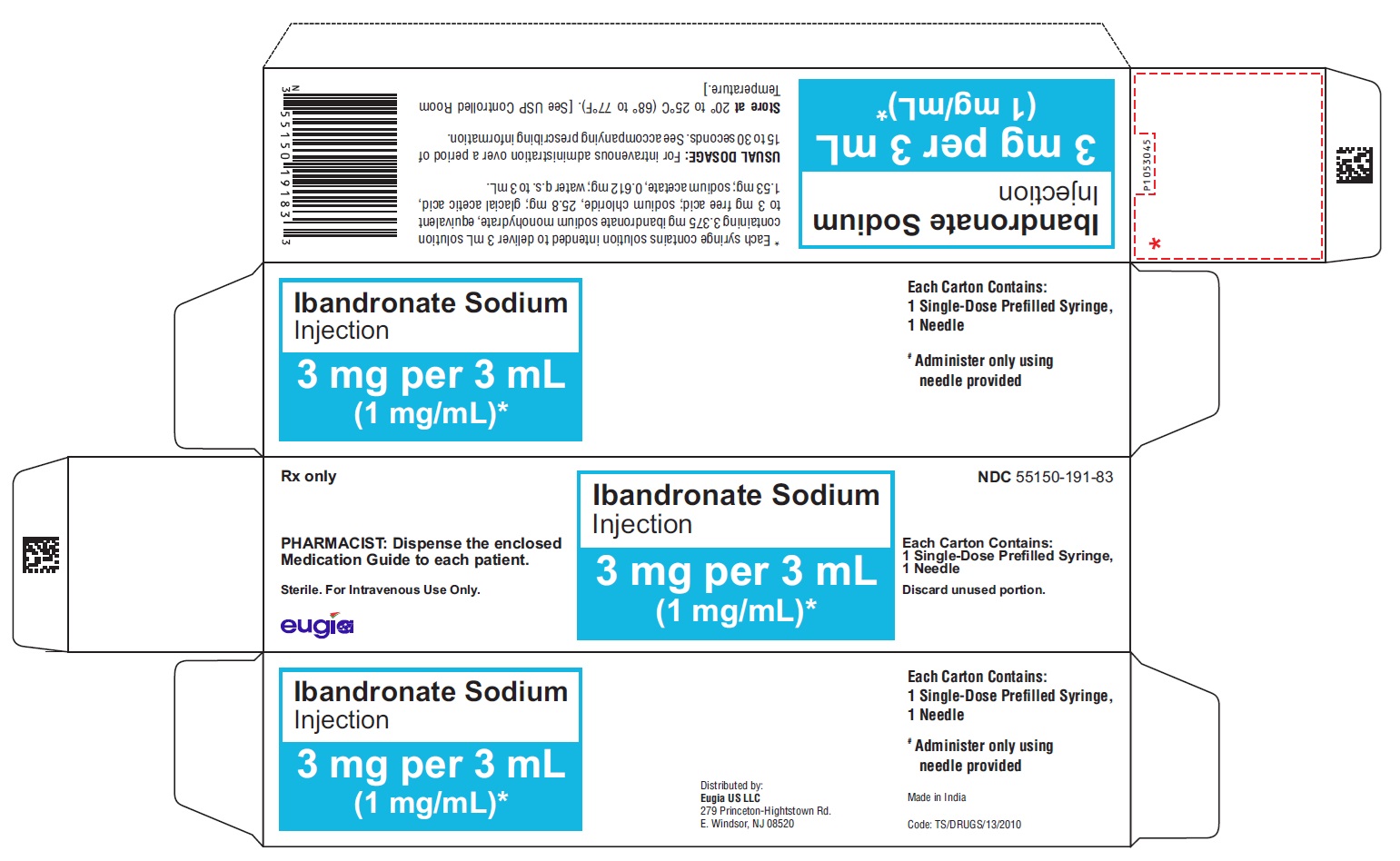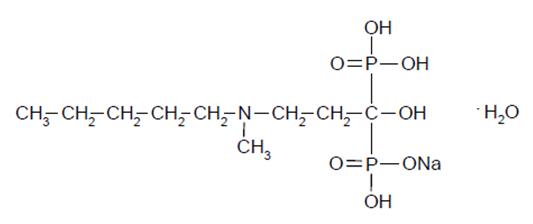 DRUG LABEL: Ibandronate Sodium
NDC: 55150-191 | Form: INJECTION, SOLUTION
Manufacturer: Eugia US LLC
Category: prescription | Type: Human Prescription Drug Label
Date: 20260127

ACTIVE INGREDIENTS: IBANDRONATE SODIUM 3 mg/3 mL
INACTIVE INGREDIENTS: ACETIC ACID; SODIUM ACETATE; SODIUM CHLORIDE; WATER

HIGHLIGHTS OF PRESCRIBING INFORMATION

These highlights do not include all the information needed to use IBANDRONATE SODIUM INJECTION safely and effectively. See full prescribing information for IBANDRONATE SODIUM INJECTION.
IBANDRONATE SODIUM injection, for intravenous use
Initial U.S. Approval: 2003

RECENT MAJOR CHANGES

Warnings and Precautions, Atypical Fractures Including Femoral Fractures (5.7) 10/2025

1 INDICATIONS AND USAGE

Ibandronate sodium injection is a bisphosphonate indicated for the treatment of osteoporosis in postmenopausal women. (1.1)
Limitations of Use
Optimal duration of use has not been determined. For patients at low-risk for fracture, consider drug discontinuation after 3 to 5 years of use (1.2)

2 DOSAGE AND ADMINISTRATION

- 3 mg every 3 months administered intravenously over a period of 15 to 30 seconds (2.2)
- Dosing Instructions:
  - Only administer intravenously by a health care professional. (2.1)
  - Do not mix with calcium-containing solutions or other intravenously administered drugs. (2.1)
  - Do not administer more frequently than once every 3 months. (2.2)
- Instruct patients to take supplemental calcium and vitamin D if dietary intake is inadequate

3 DOSAGE FORMS AND STRENGTHS

Ibandronate sodium injection is supplied as a kit containing:

- 3 mg/3 mL (1 mg/mL) single-dose prefilled syringe.
- 25-gauge, 3/4 inch needle with wings, needle-stick protection device, and a 9 cm plastic tubing for attachment (3)

4 CONTRAINDICATIONS

- Hypocalcemia (4)
- Hypersensitivity to ibandronate sodium injection (4)

5 WARNINGS AND PRECAUTIONS

- Hypocalcemia can worsen. Correct hypocalcemia prior to use. Adequately supplement patients with calcium and vitamin D (5.1)
- Anaphylaxis, including fatal events, has been reported. (5.2)
- Renal Toxicity may be greater in patients with underlying renal impairment. Do not administer ibandronate sodium injection to patients with severe renal impairment (creatinine clearance less than 30 mL/min). Monitor serum creatinine prior to each dose. (5.3)
- Tissue Damage with Inappropriate Drug Administration can occur. Do not administer ibandronate sodium injection intra-arterially or paravenously. (5.4)
- Osteonecrosis of the jaw (ONJ) has been reported. (5.5)
- Severe Bone, Joint, and/or Muscle Pain may occur, consider discontinuing use if symptoms occur. (5.6)
- Atypical Fractures Including Femoral Fractures have been reported. Patients with new thigh or groin pain should be evaluated to rule out a femoral fracture. Risk/benefit of continuing bisphosphonate therapy should be re-evaluated in these patients and interruption of bisphosphonate therapy should be considered. (5.7)

6 ADVERSE REACTIONS

The most frequently reported adverse reactions (>5%) are arthralgia, back pain, and abdominal pain. (6.1)
To report SUSPECTED ADVERSE REACTIONS, contact Eugia US LLC at 1-866-850-2876 or FDA at 1-800-FDA-1088 or www.fda.gov/medwatch.

FULL PRESCRIBING INFORMATION

1 INDICATIONS AND USAGE

1.1 Treatment of Postmenopausal Osteoporosis

Ibandronate sodium injection is indicated for the treatment of osteoporosis in postmenopausal women. In postmenopausal women with osteoporosis, ibandronate sodium injection increases bone mineral density (BMD) and reduces the incidence of vertebral fractures [see Clinical Studies (14)].

1.2 Important Limitations of Use

The safety and effectiveness of ibandronate sodium injection for the treatment of osteoporosis are based on clinical data of one year duration. The optimal duration of use has not been determined. All patients on bisphosphonate therapy should have the need for continued therapy re-evaluated on a periodic basis. Patients at low-risk for fracture should be considered for drug discontinuation after 3 to 5 years of use. Patients who discontinue therapy should have their risk for fracture re-evaluated periodically.

2 DOSAGE AND ADMINISTRATION

2.1 Important Administration Instructions

Ibandronate sodium injection must be administered intravenously only by a health care professional. Care must be taken not to administer intra-arterially or paravenously as this could lead to tissue damage [see Warnings and Precautions (5.4)].

- Appropriate medical support and monitoring measures should be readily available when ibandronate sodium injection is administered. If anaphylactic or other severe hypersensitivity/allergic reactions occur, immediately discontinue the injection and initiate appropriate treatment [see Warnings and Precautions (5.2)].
- Visually inspect the liquid in the prefilled syringe for particulate matter and discoloration before administration. Do not use prefilled syringes with particulate matter or discoloration.
- Administer only with the enclosed needle.
- Discard any unused portion.
- Do not mix with calcium-containing solutions or other intravenously administered drugs.
- Prefilled syringes are single-dose only.

2.2 Dosage Information

The recommended dose of ibandronate sodium injection for the treatment of postmenopausal osteoporosis is 3 mg every 3 months administered intravenously over a period of 15 to 30 seconds. Do not administer more frequently than once every 3 months.

2.3 Laboratory Testing and Oral Examination Prior to Administration

Prior to administration of each dose obtain a serum creatinine [see Warnings and Precautions (5.3)]. Given that bisphosphonates have been associated with osteonecrosis of the jaw (ONJ), perform a routine oral examination prior to administration of ibandronate sodium injection.

2.4 Calcium and Vitamin D Supplementation

Instruct patients to take supplemental calcium and vitamin D if their dietary intake is inadequate [see Warnings and Precautions (5.1)].

2.5 Dosing After Missed Dose

If the dose is missed, administer as soon as it can be re-scheduled. Thereafter, ibandronate sodium injection should be scheduled every 3 months from the date of the last injection.

2.6 Dosage Modifications in Patients with Renal Impairment

Do not administer to patients with severe renal impairment (creatinine clearance less than 30 mL/minute) [see Warnings and Precautions (5.3) and CLINICAL PHARMACOLOGY (12.3)]. No dose adjustment is necessary for patients with mild or moderate renal impairment (creatinine clearance greater than or equal to 30 mL/min) [see CLINICAL PHARMACOLOGY (12.3)].

3 DOSAGE FORMS AND STRENGTHS

Ibandronate sodium injection is supplied as a kit containing:

- 3 mg/3 mL (1 mg/mL) single-dose prefilled syringe.
- 25-gauge, 3/4 inch needle with wings, needle-stick protection device, and a 9 cm plastic tubing for attachment

4 CONTRAINDICATIONS

Ibandronate sodium injection is contraindicated in patients with the following conditions:

- Hypocalcemia [see Warnings and Precautions (5.1)]
- Known hypersensitivity to ibandronate sodium injection or to any of its excipients. Cases of anaphylaxis, including fatal events, have been reported [see Warnings and Precautions (5.2), Adverse Reactions (6.2)]

5 WARNINGS AND PRECAUTIONS

5.1 Hypocalcemia and Mineral Metabolism

Ibandronate sodium injection may cause a decrease in serum calcium values. Treat hypocalcemia, hypovitaminosis D, and other disturbances of bone and mineral metabolism before starting ibandronate sodium injection therapy.
Adequate intake of calcium and vitamin D is important in all patients. It is recommended that patients receive supplemental calcium and vitamin D if dietary intake is inadequate.

5.2 Anaphylactic Reaction

Cases of anaphylaxis, including fatal events, have been reported in patients treated with ibandronate sodium injection.
Appropriate medical support and monitoring measures should be readily available when ibandronate sodium injection is administered. If anaphylactic or other severe hypersensitivity/allergic reactions occur, immediately discontinue the injection and initiate appropriate treatment.

5.3 Renal Impairment

Treatment with intravenous bisphosphonates has been associated with renal toxicity manifested as deterioration in renal function and acute renal failure. Although no cases of acute renal failure were observed in controlled clinical trials in which intravenous ibandronate was administered as a 15- to 30-second bolus, acute renal failure has been reported postmarketing. Do not administer ibandronate sodium injection to patients with severe renal impairment (creatinine clearance less than 30 mL/min).
Obtain serum creatinine prior to each ibandronate sodium injection. After ibandronate sodium injection, assess renal function, as clinically appropriate, in patients with concomitant diseases or taking medications that have the potential for adverse effects on the kidney. Ibandronate sodium injection should be withheld in patients with renal deterioration.

5.4 Tissue Damage Related to Inappropriate Drug Administration

Ibandronate sodium injection must only be administered intravenously. Care must be taken not to administer ibandronate sodium injection intra-arterially or paravenously as this could lead to tissue damage.
Do not administer ibandronate sodium injection by any other route of administration. The safety and efficacy of ibandronate sodium injection following non-intravenous routes of administration have not been established.

5.5 Osteonecrosis of the Jaw

Osteonecrosis of the jaw (ONJ) has been reported in patients treated with bisphosphonates, including ibandronate sodium injection. Most cases have been in cancer patients treated with intravenous bisphosphonates undergoing dental procedures. Some cases have occurred in patients with postmenopausal osteoporosis treated with either oral or intravenous bisphosphonates. A routine oral examination should be performed by the prescriber prior to initiation of bisphosphonate treatment. Consider a dental examination with appropriate preventive dentistry prior to treatment with bisphosphonates in patients with a history of concomitant risk factors (e.g., cancer, chemotherapy, angiogenesis inhibitors, radiotherapy, corticosteroids, poor oral hygiene, pre-existing dental disease or infection, anemia, coagulopathy). Concomitant administration of drugs associated with ONJ may increase the risk of developing ONJ. The risk of ONJ may increase with duration of exposure to bisphosphonates.

While on treatment, patients with concomitant risk factors should avoid invasive dental procedures if possible. For patients who develop ONJ while on bisphosphonate therapy, dental surgery may exacerbate the condition. For patients requiring dental procedures, there are no data available to suggest whether discontinuation of bisphosphonate treatment reduces the risk of ONJ. The clinical judgment of the treating physician should guide the management plan of each patient based on individual benefit/risk assessment [see Adverse Reactions (6.1)].

5.6 Musculoskeletal Pain

Severe and occasionally incapacitating bone, joint, and/or muscle pain has been reported in patients taking ibandronate and other bisphosphonates [see Adverse Reactions (6.2)]. The time to onset of symptoms varied from one day to several months after starting the drug. Most patients had relief of symptoms after stopping the bisphosphonate. A subset of patients had recurrence of symptoms when rechallenged with the same drug or another bisphosphonate. Discontinue ibandronate if severe symptoms develop.

5.7 Atypical Fractures Including Femoral Fractures

Atypical, low-energy, or low trauma fractures of the femoral shaft have been reported during treatment with bisphosphonates, including ibandronate sodium in patients with osteoporosis. Atypical femur and other fractures most commonly occur with minimal or no trauma to the affected area. These fractures occurred anywhere in the femoral shaft from just below the lesser trochanter to above the supracondylar flare and are traverse or short oblique in orientation without evidence of comminution. Atypical fractures of other bones have also been reported. They may be bilateral. These fractures can also occur in osteoporotic patients who have not been treated with bisphosphonates. Concomitant treatment with glucocorticoids may also induce these fractures.

Prodromal pain in the affected area, usually presenting as dull, aching thigh pain, weeks to months before a complete fracture occurs was reported by patients.

Any patient with a history of bisphosphonate exposure who presents with thigh or groin pain should be suspected of having an atypical fracture and should be evaluated to rule out an incomplete femur fracture. Bony pain in other locations should also be considered for evaluation of atypical fracture. Patients presenting with an atypical fracture should also be assessed for symptoms and signs of fracture in the contralateral limb. Risk/benefit of continuing bisphosphonate therapy should be re-evaluated in these patients and interruption of bisphosphonate therapy should be considered.

6 ADVERSE REACTIONS

The following clinically significant adverse drug reactions are described elsewhere in the labeling:

- Hypocalcemia and Mineral Metabolism [see Warnings and Precautions (5.1)]
- Anaphylactic Reaction [see Warnings and Precautions (5.2)]
- Renal Impairment [see Warnings and Precautions (5.3)]
- Tissue Damage Related to Inappropriate Drug Administration [see Warnings and Precautions (5.4)]
- Osteonecrosis of the Jaw [see Warnings and Precautions (5.5)]
- Musculoskeletal Pain [see Warnings and Precautions (5.6)]
- Atypical Fractures Including Femoral Fractures [see Warnings and Precautions (5.7)]

6.1 Clinical Trials Experience

Because clinical trials are conducted under widely varying conditions, adverse reaction rates observed in the clinical trials of a drug cannot be directly compared to rates in the clinical trials of another drug and may not reflect the rates observed in practice.
Quarterly Intravenous Injection –
In a 1-year, double-blind, multicenter study comparing ibandronate sodium injection administered intravenously as 3 mg every 3 months to ibandronate 2.5 mg daily oral tablet in women with postmenopausal osteoporosis, the overall safety and tolerability profiles of the two dosing regimens were similar. The incidence of serious adverse reactions was 8% in the ibandronate 2.5 mg daily group and 7.5% in the ibandronate sodium injection 3 mg once every 3 months group. The percentage of patients who withdrew from treatment due to adverse reactions was approximately 6.7% in the ibandronate 2.5 mg daily group and 8.5% in the ibandronate sodium injection 3 mg every 3 months group. Table 1 lists the adverse reactions reported in greater than 2% of patients.

Table 1 Adverse Reactions With an Incidence of at Least 2% in Patients Treated with Ibandronate Sodium Injection (3 mg once every 3 months) or Ibandronate Daily Oral Tablet (2.5 mg)
Body System/Adverse Reaction | Ibandronate 2.5 mg Daily (Oral) % (n = 465) | Ibandronate Sodium Injection 3 mg every 3 months (Intravenous) % (n = 469)
Infections and Infestations
Influenza | 8 | 5
Nasopharyngitis | 6 | 3
Cystitis | 3 | 2
Gastroenteritis | 3 | 2
Urinary Tract Infection | 3 | 3
Bronchitis | 3 | 2
Upper Respiratory Tract Infection | 3 | 1
Gastrointestinal Disorders
Abdominal Pain* | 6 | 5
Dyspepsia | 4 | 4
Nausea | 4 | 2
Constipation | 4 | 3
Diarrhea | 2 | 3
Gastritis | 2 | 2
Musculoskeletal and Connective Tissue Disorders
Arthralgia | 9 | 10
Back Pain | 8 | 7
Localized Osteoarthritis | 2 | 2
Pain in Extremity | 2 | 3
Myalgia | 1 | 3
Nervous System Disorders
Dizziness | 3 | 2
Headache | 3 | 4
Psychiatric Disorders
Insomnia | 3 | 1
Depression | 2 | 1
General Disorders and Administration Site Conditions
Influenza-like Illness† | 1 | 5
Fatigue | 1 | 3
Skin and Subcutaneous Tissue Disorders
Rash‡ | 3 | 2
* Combination of abdominal pain and abdominal pain upper
† Combination of influenza-like illness and acute phase reaction
‡ Combination of rash, rash pruritic, rash macular, dermatitis, dermatitis allergic, exanthema, erythema, rash papular, rash generalized, dermatitis medicamentosa, rash erythematous

Acute Phase Reaction-like Events
Symptoms consistent with acute phase reaction (APR) have been reported with intravenous bisphosphonate use. The overall incidence of patients with APR-like events was higher in the intravenous treatment group (4% in the ibandronate 2.5 mg daily oral tablet group vs. 10% in the ibandronate sodium injection 3 mg once every 3 months group). These incidence rates are based upon reporting of any of 33 potential APR-like symptoms within 3 days of an intravenous dose and lasting 7 days or less. In most cases, no specific treatment was required and the symptoms subsided within 24 to 48 hours.
Injection Site Reactions
Local reactions at the injection site, such as redness or swelling, were observed at a higher incidence in patients treated with ibandronate sodium injection 3 mg every 3 months (1.7%; 8/469) than in patients treated with placebo injections (0.2%; 1/465). In most cases, the reaction was of mild to moderate severity.
Daily Oral Tablet -
The safety of ibandronate 2.5 mg once daily in the treatment and prevention of postmenopausal osteoporosis was assessed in 3577 patients aged 41 to 82 years. The duration of the trials was 2 to 3 years, with 1134 patients exposed to placebo and 1140 exposed to ibandronate 2.5 mg. Patients with pre-existing gastrointestinal disease and concomitant use of non-steroidal anti-inflammatory drugs, proton pump inhibitors and H2 antagonists were included in these clinical trials. All patients received 500 mg calcium plus 400 international units vitamin D supplementation daily.
The incidence of all-cause mortality was 1% in the placebo group and 1.2% in the ibandronate 2.5 mg daily group. The incidence of serious adverse reactions was 20% in the placebo group and 23% in the ibandronate 2.5 mg daily oral tablet group. The percentage of patients who withdrew from treatment due to adverse reactions was approximately 17% in both the placebo group and the ibandronate 2.5 mg daily oral tablet group. Table 2 lists adverse reactions from the Treatment and Prevention Studies reported in greater than or equal to 2% of patients and in more patients treated with ibandronate 2.5 mg daily oral tablet than patients treated with placebo.

Table 2 Adverse Reactions Occurring at an Incidence greater than or equal to 2% and in More Patients Treated with Ibandronate 2.5 mg Daily Oral Tablet than in Patients Treated with Placebo in the Osteoporosis Treatment and Prevention Studies
Body System | Placebo % (n = 1134) | Ibandronate 2.5 mg daily % (n = 1140)
Body as a Whole
Back Pain | 12 | 14
Pain in Extremity | 6 | 8
Asthenia | 2 | 4
Allergic Reaction | 2 | 3
Digestive System
Dyspepsia | 10 | 12
Diarrhea | 5 | 7
Tooth Disorder | 2 | 4
Vomiting | 2 | 3
Gastritis | 2 | 2
Musculoskeletal System
Myalgia | 5 | 6
Joint Disorder | 3 | 4
Arthritis | 3 | 3
Nervous System
Headache | 6 | 7
Dizziness | 3 | 4
Vertigo | 3 | 3
Respiratory System
Upper Respiratory Infection | 33 | 34
Bronchitis | 7 | 10
Pneumonia | 4 | 6
Pharyngitis | 2 | 3
Urogenital System
Urinary Tract Infection | 4 | 6

Gastrointestinal Adverse Reactions
The incidence of selected gastrointestinal adverse reactions in the placebo and ibandronate 2.5 mg daily groups were: dyspepsia (10% vs. 12%), diarrhea (5% vs. 7%), and abdominal pain (5% vs. 6%).
Musculoskeletal Adverse Reactions
The incidence of selected musculoskeletal adverse reactions in the placebo and ibandronate 2.5 mg daily groups were: back pain (12% vs. 14%), arthralgia (14% vs. 14%) and myalgia (5% vs. 6%).

6.2 Postmarketing Experience

The following adverse reactions have been identified during post-approval use of ibandronate sodium injection or bisphosphonate products. Because these reactions are reported voluntarily from a population of uncertain size, it is not always possible to reliably estimate their frequency or establish a causal relationship to drug exposure.

Hypersensitivity: Allergic reactions including anaphylaxis with fatalities, angioedema, asthma exacerbation, bronchospasm, rash, Stevens-Johnson syndrome, erythema multiforme, and dermatitis bullous [see Contraindications (4), Warnings and Precautions (5.2)].

Hypocalcemia: Hypocalcemia [see Warnings and Precautions (5.1)].

Renal Toxicity: Acute renal failure [see Warnings and Precautions (5.3)].

Osteonecrosis of the Jaw: Osteonecrosis of the jaw and other oro-facial sites, including the external auditory canal [see Warnings and Precautions (5.5)].

Musculoskeletal: Bone, joint, or muscle pain, described as severe or incapacitating, have been reported rarely [see Warnings and Precautions (5.6)]; low-energy femoral shaft and subtrochanteric fractures, and atypical fractures of other bones [see Warnings and Precautions (5.7)].

Eye Inflammation: Iritis and uveitis. In some cases with other bisphosphonates, these events did not resolve until the bisphosphonate was discontinued.

7 DRUG INTERACTIONS

7.1 Melphalan/Prednisolone

Intravenous ibandronate (6 mg) did not interact with intravenous melphalan (10 mg/m^2) or oral prednisolone (60 mg/m^2). [See Clinical Pharmacology (12.3)]

7.2 Tamoxifen

There was no interaction between oral 30 mg tamoxifen and intravenous 2 mg ibandronate. [see Clinical Pharmacology (12.3)]

7.3 Bone Imaging Agents

Bisphosphonates are known to interfere with the use of bone-imaging agents. Specific studies with ibandronate have not been performed.

8 USE IN SPECIFIC POPULATIONS

8.1 Pregnancy

Risk Summary
Ibandronate is not indicated for use in women of reproductive potential. There are no data with ibandronate use in pregnant women to inform any drug-associated risks.
In reproductive toxicity studies in the rat, ibandronate caused obstruction of labor, with maternal periparturient mortality, pup loss and reduced pup weight at greater than or equal to 2 times human exposure at the recommended human intravenous dose of 3 mg. Abnormal pup odontogeny was observed at greater than or equal to 18 times human exposure. In rats dosed during pregnancy, kidney developmental toxicity occurred in offspring at greater than or equal to 47 times human exposure. Also, fetal weight and pup growth were reduced at greater than or equal to 5 times human exposure. In reproductive studies in the rabbit, ibandronate caused maternal mortality, reduced maternal body weight gain, decreased litter size due to increased resorption rate, and decreased fetal weight at 19 times the recommended human dose (see Data).
Data
Animal Data
In pregnant rats given intravenous doses producing greater than or equal to 2 times human exposure from Day 17 post-coitum until Day 20 post-partum, ibandronate treatment resulted in dystocia, maternal mortality, and early postnatal pup loss in all dose groups. Reduced body weight at birth was observed at greater than or equal to 4 times the human exposure. Pups exhibited abnormal odontogeny that decreased food consumption and body weight gain at greater than or equal to 18 times human exposure. Periparturient mortality has also been observed with other bisphosphonates and appears to be a class effect related to inhibition of skeletal calcium mobilization resulting in hypocalcemia and dystocia.
Exposure of pregnant rats during the period of organogenesis resulted in an increased fetal incidence of RPU (renal pelvis ureter) syndrome at an intravenous dose producing greater than or equal to 47 times human exposure. In this spontaneous delivery study, dystocia was counteracted by perinatal calcium supplementation. In rat studies with intravenous dosing during gestation, fetal weight and pup growth were reduced at doses producing greater than or equal to 5 times human exposure.
In pregnant rabbits given intravenous doses during the period of organogenesis, maternal mortality, reduced maternal body weight gain, decreased litter size due to increased resorption rate, and decreased fetal weight were observed at 19 times the recommended human intravenous dose.
Exposure multiples for the rat studies were calculated using human exposure at the recommended intravenous dose of 3 mg every 3 months and were based on cumulative area under the curve (AUC) comparison. Exposure multiples for the rabbit study were calculated for the recommended human intravenous dose of 3 mg every 3 months and were based on cumulative dose/[body surface area] comparison. Doses in pregnant animals were 0.05, 0.1, 0.15, 0.3, 0.5 or 1 mg/kg/day in rats, and 0.03, 0.07, or 0.2 mg/kg/day in rabbits.

8.2 Lactation

Risk Summary
Ibandronate is not indicated for use in women of reproductive potential. There is no information on the presence of ibandronate in human milk, the effects of ibandronate on the breastfed infant, or the effects of ibandronate on milk production. Ibandronate is present in rat milk (see Data). The clinical relevance of this data is unclear.
Data
Animal Data
In lactating rats treated with intravenous doses of 0.08 mg/kg, ibandronate was present in breast milk at concentrations of 8.1 to 0.4 ng/mL from 2 to 24 hours after dose administration. Concentrations in milk averaged 1.5 times plasma concentrations.

8.4 Pediatric Use

Safety and effectiveness of ibandronate in pediatric patients have not been established.

8.5 Geriatric Use

Of the patients receiving ibandronate sodium injection 3 mg every 3 months for 1 year, 51% were over 65 years of age. No overall differences in effectiveness or safety were observed between these patients and younger patients, but greater sensitivity in some older individuals cannot be ruled out.

8.6 Renal Impairment

Ibandronate sodium injection should not be administered to patients with severe renal impairment (creatinine clearance less than 30 mL/min) [see Warnings and Precautions (5.3)].

10 OVERDOSAGE

No cases of overdose were reported in premarketing studies with ibandronate sodium injection. Overdosage with intravenous bisphosphonates may result in hypocalcemia, hypophosphatemia, and hypomagnesemia. Clinically relevant reductions in serum levels of calcium, phosphorus, and magnesium should be corrected by intravenous administration of calcium gluconate, potassium or sodium phosphate, and magnesium sulfate, respectively.
Dialysis would not be beneficial unless it is administered within 2 hours following the overdose.

11 DESCRIPTION

Ibandronate sodium is a nitrogen-containing bisphosphonate that inhibits osteoclast-mediated bone resorption. The chemical name for ibandronate sodium is 3-(N-methyl-N-pentyl)amino-1-hydroxypropane-1,1-diphosphonic acid, monosodium salt, monohydrate with the molecular formula C9H22NO7P2Na•H2O and a molecular weight of 359.24. Ibandronate sodium is a white to almost white powder. It is freely soluble in water and practically insoluble in organic solvents. Ibandronate sodium has the following structural formula:
Ibandronate sodium injection is intended for intravenous administration only. Ibandronate sodium injection is available as a sterile, clear, colorless, ready-to-use solution free from visible particles in a prefilled syringe that delivers 3.375 mg of ibandronate monosodium salt monohydrate in 3 mL of solution, equivalent to a dose of 3 mg ibandronate free acid. Inactive ingredients include glacial acetic acid (1.53 mg), sodium acetate trihydrate (0.612 mg), sodium chloride (25.8 mg) and water (q.s. to 3 mL). Glacial acetic acid and sodium acetate trihydrate are used to adjust pH.

12 CLINICAL PHARMACOLOGY

12.1 Mechanism of Action

The action of ibandronate on bone is based on its affinity for hydroxyapatite, which is part of the mineral matrix of bone. Ibandronate inhibits osteoclast activity and reduces bone resorption and turnover. In postmenopausal women, it reduces the elevated rate of bone turnover, leading to, on average, a net gain in bone mass.

12.2 Pharmacodynamics

In studies of postmenopausal women, ibandronate sodium injection at doses of 0.5 mg to 3 mg produced biochemical changes indicative of inhibition of bone resorption, including decreases of biochemical markers of bone collagen degradation (cross-linked C-telopeptide of Type I collagen [CTX]). Changes in markers of bone formation (osteocalcin) were observed later than changes in resorption markers, as expected, due to the coupled nature of bone resorption and formation.
Year 1 results from an efficacy and safety study comparing ibandronate sodium injection 3 mg every 3 months and ibandronate 2.5 mg daily oral tablet demonstrated that both dosing regimens significantly suppressed serum CTX levels at Months 3, 6, and 12. The median pre-dose or trough serum CTX levels in the intent-to-treat population reached a nadir of 57% (ibandronate sodium injection) and 62% (ibandronate 2.5 mg tablets) below baseline values by Month 6, and remained stable at Month 12 of treatment.

12.3 Pharmacokinetics

Distribution
Area under the serum ibandronate concentrations versus time curve increases in a dose proportional manner after administration of 2 mg to 6 mg by intravenous injection.
After administration, ibandronate either rapidly binds to bone or is excreted into urine. In humans, the apparent terminal volume of distribution is at least 90 L, and the amount of dose removed from the circulation into the bone is estimated to be 40% to 50% of the circulating dose. In one study, in vitro protein binding in human serum was approximately 86% over an ibandronate concentration range of 20 to 2,000 ng/mL (approximate range of maximum serum ibandronate concentrations upon intravenous bolus administration).
Metabolism
There is no evidence that ibandronate is metabolized in humans. Ibandronate does not inhibit human P450 1A2, 2A6, 2C9, 2C19, 2D6, 2E1, and 3A4 isozymes in vitro.
Ibandronate does not undergo hepatic metabolism and does not inhibit the hepatic cytochrome P450 system. Ibandronate is eliminated by renal excretion. Based on a rat study, the ibandronate secretory pathway does not appear to include known acidic or basic transport systems involved in the excretion of other drugs.
Elimination
The portion of ibandronate that is not removed from the circulation via bone absorption is eliminated unchanged by the kidney (approximately 50% to 60% of the administered intravenous dose).
The plasma elimination of ibandronate is multiphasic. Its renal clearance and distribution into bone accounts for a rapid and early decline in plasma concentrations, reaching 10% of Cmax within 3 or 8 hours after intravenous or oral administration, respectively. This is followed by a slower clearance phase as ibandronate redistributes back into the blood from bone. The observed apparent terminal half-life for ibandronate is generally dependent on the dose studied and on assay sensitivity. The observed apparent terminal half-life for intravenous 2 and 4 mg ibandronate after 2 hours of infusion ranges from 4.6 to 15.3 hours and 5 to 25.5 hours, respectively.
Following intravenous administration, total clearance of ibandronate is low, with average values in the range 84 to 160 mL/min. Renal clearance (about 60 mL/min in healthy postmenopausal women) accounts for 50% to 60% of total clearance and is related to creatinine clearance. The difference between the apparent total and renal clearances likely reflects bone uptake of the drug.
Pharmacokinetics in Specific Populations
Pediatrics
The pharmacokinetics of ibandronate have not been studied in patients less than 18 years of age.
Gender
The pharmacokinetics of ibandronate are similar in both men and women.
Geriatric
Since ibandronate is not known to be metabolized, the only difference in ibandronate elimination for geriatric patients versus younger patients is expected to relate to progressive age-related changes in renal function [see Use in Specific Populations (8.5)].
Race
Pharmacokinetic differences due to race have not been studied.
Renal Impairment
Renal clearance of ibandronate in patients with various degrees of renal impairment is linearly related to creatinine clearance (CLcr).
Following a single dose of 0.5 mg ibandronate by intravenous administration, patients with creatinine clearance 40 to 70 mL/min had 55% higher exposure (AUC∞) than the exposure observed in patients with creatinine clearance higher than 90 mL/min. Patients with severe renal impairment (creatinine clearance below 30 mL/min) had more than a two-fold increase in exposure compared to the exposure for patients with creatinine clearance equal to or higher than 80 mL/min [see Dosage and Administration (2.6) and Use in Specific Populations (8.6)].
Hepatic Impairment
No studies have been performed to assess the pharmacokinetics of ibandronate in patients with hepatic impairment since ibandronate is not metabolized in the human liver.
Drug Interaction
Melphalan/Prednisolone
A pharmacokinetic interaction study in multiple myeloma patients demonstrated that intravenous melphalan (10 mg/m^2) and oral prednisolone (60 mg/m^2) did not interact with 6 mg ibandronate upon intravenous coadministration. Ibandronate did not interact with melphalan or prednisolone.
Tamoxifen
A pharmacokinetic interaction study in healthy postmenopausal women demonstrated that there was no interaction between oral 30 mg tamoxifen and intravenous 2 mg ibandronate.

13 NONCLINICAL TOXICOLOGY

13.1 Carcinogenesis, Mutagenesis, Impairment of Fertility

Carcinogenesis
In a 104-week carcinogenicity study, doses of 3, 7, or 15 mg/kg/day were administered by oral gavage to Wistar rats (systemic exposures in males and females up to 3 and 1 times, respectively, human exposure). There were no significant drug-related tumor findings in male or female rats. In a 78-week carcinogenicity study, doses of 5, 20, or 40 mg/kg/day were administered by oral gavage to NMRI mice (exposures in males and females up to 96 and 14 times, respectively, human exposure). There were no significant drug-related tumor findings in male or female mice. In a 90-week carcinogenicity study, doses of 5, 20, or 80 mg/kg/day were administered in the drinking water to NMRI mice. A dose-related increased incidence of adrenal subcapsular adenoma/carcinoma was observed in female mice, which was statistically significant at 80 mg/kg/day (32 to 51 times human exposure). The relevance of these findings to humans is unknown.
Exposure multiples comparing human and rodent doses were calculated using human exposure at the recommended intravenous dose of 3 mg every 3 months, based on cumulative AUC comparison.
Mutagenesis
There was no evidence for a mutagenic or clastogenic potential of ibandronate in the following assays: in vitro bacterial mutagenesis assay in Salmonella typhimurium and Escherichia coli (Ames test), mammalian cell mutagenesis assay in Chinese hamster V79 cells, and chromosomal aberration test in human peripheral lymphocytes, each with and without metabolic activation. Ibandronate was not genotoxic in the in vivo mouse micronucleus tests for chromosomal damage.
Impairment of Fertility
In female rats treated from 14 days prior to mating through gestation, decreases in fertility, corpora lutea and implantation sites, and increased preimplantation loss were observed at an intravenous dose of 1.2 mg/kg/day (117 times human exposure). In male rats treated for 28 days prior to mating, a decrease in sperm production and altered sperm morphology were observed at intravenous doses greater than or equal to 0.3 mg/kg/day (greater than or equal to 40 times human exposure).
Exposure multiples comparing human and rat doses were calculated using human exposure at the recommended intravenous dose of 3 mg every 3 months, based on cumulative AUC comparison.

13.2 Animal Pharmacology

Animal studies have shown that ibandronate is an inhibitor of osteoclast-mediated bone resorption. In the Schenk assay in growing rats, ibandronate inhibited bone resorption and increased bone volume, based on histologic examination of the tibial metaphyses. There was no evidence of impaired mineralization at the highest dose of 5 mg/kg/day (subcutaneously), which is 1000 times the lowest antiresorptive dose of 0.005 mg/kg/day in this model, and 5000 times the optimal antiresorptive dose of 0.001 mg/kg/day in the aged ovariectomized rat. This indicates that ibandronate sodium injection administered at a therapeutic dose is unlikely to induce osteomalacia.
Long-term daily or intermittent administration of ibandronate to ovariectomized rats or monkeys was associated with suppression of bone turnover and increases in bone mass. Vertebral BMD, trabecular density, and biomechanical strength were increased dose-dependently in rats and monkeys, at doses up to 8 to 4 times the human intravenous dose of 3 mg every 3 months, based on cumulative dose normalized for body surface area (mg/m^2) and area under the curve (AUC) comparison, respectively. Ibandronate maintained the positive correlation between bone mass and strength at the ulna and femoral neck. New bone formed in the presence of ibandronate had normal histologic structure and did not show mineralization defects.

14 CLINICAL STUDIES

14.1 Treatment of Postmenopausal Osteoporosis

Quarterly Intravenous Injection

The effectiveness and safety of ibandronate sodium injection 3 mg once every 3 months were demonstrated in a randomized, double-blind, multinational, noninferiority study in 1358 women with postmenopausal osteoporosis (L2-L4 lumbar spine BMD, T-score below -2.5 SD at baseline). The control group received ibandronate 2.5 mg daily oral tablets. The primary efficacy parameter was the relative change from baseline to 1 year of treatment in lumbar spine BMD, which was compared between the intravenous injection and the daily oral treatment groups. All patients received 400 international units vitamin D and 500 mg calcium supplementation per day.

Effect on BMD

In the intent-to-treat (ITT) efficacy analysis, the least-squares mean increase at 1 year in lumbar spine BMD in patients (n = 429) treated with ibandronate sodium injection 3 mg once every 3 months (4.5%) was statistically superior to that in patients (n = 434) treated with daily oral tablets (3.5%). The mean difference between groups was 1.1% (95% confidence interval: 0.5%, 1.6%; p<0.001; see Figure 1). The mean increase from baseline in total hip BMD at 1 year was 2.1% in the ibandronate sodium injection 3 mg once every 3 months group and 1.5% in the ibandronate 2.5 mg daily oral tablet group. Consistently higher BMD increases at the femoral neck and trochanter were also observed following ibandronate sodium injection 3 mg once every 3 months compared to ibandronate 2.5 mg daily oral tablet.

Figure 1 Mean Percent Change (95% Confidence Interval) from Baseline in Lumbar Spine BMD at One Year in Patients Treated with Ibandronate 2.5 mg Daily Oral Tablet or Ibandronate Sodium Injection 3 mg Once Every 3 Months

Bone Histology

The histological analysis of bone biopsies after 22 months of treatment with 3 mg intravenous ibandronate every 3 months (n = 30) or 23 months of treatment with 2 mg intravenous ibandronate every 2 months (n = 27) in women with postmenopausal osteoporosis showed bone of normal quality and no indication of a mineralization defect.

Daily Oral Tablets

The effectiveness and safety of ibandronate daily oral tablets were demonstrated in a randomized, double-blind, placebo-controlled, multinational study (Treatment Study) of 2946 women aged 55 to 80 years, who were on average 21 years postmenopause, who had a lumbar spine BMD 2 to 5 SD below the premenopausal mean (T-score) in at least one vertebra [L1-L4], and who had one to four prevalent vertebral fractures. Ibandronate was evaluated at oral doses of 2.5 mg daily and 20 mg intermittently. The main outcome measure was the occurrence of new radiographically diagnosed, vertebral fractures after 3 years of treatment. The diagnosis of an incident vertebral fracture was based on both qualitative diagnosis by the radiologist and quantitative morphometric criterion. The morphometric criterion required the dual occurrence of two events: a relative height ratio or relative height reduction in a vertebral body of at least 20%, together with at least a 4 mm absolute decrease in height. All women received 400 international units vitamin D and 500 mg calcium supplementation per day.

Effect on Vertebral Fracture

Ibandronate 2.5 mg daily oral tablet significantly reduced the incidence of new vertebral fractures compared to placebo. Over the course of the 3-year study, the risk for new vertebral fracture was 9.6% in the placebo-treated women and 4.7% in the women treated with ibandronate 2.5 mg daily oral tablet (p<0.001) (see Table 3).

Table 3 Effect of Ibandronate Daily Oral Tablet on the Incidence of Vertebral Fracture in the 3-Year Osteoporosis Treatment Study*
 | Proportion of Patients with Fracture (%)
 | Placebo n = 975 | Ibandronate 2.5 mg Daily n = 977 | Absolute Risk Reduction (%) 95% CI | Relative Risk Reduction (%) 95% CI
New Vertebral Fracture 0 to 3 Year | 9.6 | 4.7 | 4.9 (2.3, 7.4) | 52** (29, 68)
New and Worsening Vertebral Fracture*** 0 to 3 Year | 10.4 | 5.1 | 5.3 (2.6, 7.9) | 52 (30, 67)
Clinical (Symptomatic) Vertebral Fracture 0 to 3 Year | 5.3 | 2.8 | 2.5 (0.6, 4.5) | 49 (14, 69)
* The endpoint value is the value at the study’s last time point, 3 years, for all patients who had a fracture identified at that time; otherwise, the last postbaseline value prior to the study’s last time point is used.
** p = 0.0003 vs. placebo
*** “Worsening vertebral fracture” defined as a new fracture in a vertebral body with a prevalent fracture

Effect on Nonvertebral Fractures

Ibandronate 2.5 mg daily did not reduce the incidence of nonvertebral fractures (secondary efficacy measure). There was a similar number of nonvertebral osteoporotic fractures at 3 years reported in women treated with ibandronate 2.5 mg daily oral tablet [9.1%, (95% CI: 7.1%, 11.1%)] and placebo [8.2%, (95% CI: 6.3%, 10.2%)]. The two treatment groups were also similar with regard to the number of fractures reported at the individual non-vertebral sites: pelvis, femur, wrist, forearm, rib, and hip.

Effect on BMD

Ibandronate 2.5 mg daily oral tablet significantly increased BMD at the lumbar spine and hip relative to treatment with placebo. In the 3-year osteoporosis treatment study, ibandronate 2.5 mg daily oral tablet produced increases in lumbar spine BMD that were progressive over 3 years of treatment and were statistically significant relative to placebo at 6 months and at all later time points. Lumbar spine BMD increased by 6.4% after 3 years of treatment with ibandronate 2.5 mg daily oral tablet compared with 1.4% in the placebo group (p<0.0001). Table 4 displays the significant increases in BMD seen at the lumbar spine, total hip, femoral neck, and trochanter compared to placebo.

Table 4 Mean Percent Change in BMD from Baseline to Endpoint in Patients Treated with Ibandronate 2.5 mg Daily Oral Tablet or Placebo in the 3-Year Osteoporosis Treatment Study*
 | Placebo | Ibandronate 2.5 mg
Lumbar Spine | 1.4 (n = 693) | 6.4 (n = 712)
Total Hip | -0.7 (n = 638) | 3.1 (n = 654)
Femoral Neck | -0.7 (n = 683) | 2.6 (n = 699)
Trochanter | 0.2 (n = 683) | 5.3 (n = 699)
* The endpoint value is the value at the study’s last time point, 3 years, for all patients who had BMD measured at that time; otherwise the last postbaseline value prior to the study’s last time point is used.

Bone Histology
The effects of ibandronate 2.5 mg daily oral tablet on bone histology were evaluated in iliac crest biopsies from 16 women after 22 months of treatment and 20 women after 34 months of treatment. The histological analysis of bone biopsies showed bone of normal quality and no indication of osteomalacia or a mineralization defect.

16 HOW SUPPLIED/STORAGE AND HANDLING

16.1 How Supplied

Ibandronate sodium injection is supplied as a kit containing:

- a 3 mg/3 mL (1 mg/mL) single-dose prefilled syringe.
- a 25-gauge, 3/4 inch needle with wings, needle-stick protection device, and a 9 cm plastic tubing for attachment.

3 mg per 3 mL (1 mg/mL):
3 mL Single-Dose Prefilled Syringes,
Packaged in a carton with 1 needle NDC 55150-191-83

16.2 Storage and Handling

Store at 20° to 25°C (68° to 77°F) [see USP Controlled Room Temperature].

17 PATIENT COUNSELING INFORMATION

“See FDA-approved patient labeling (Medication Guide)”
Inform patients that ibandronate sodium injection must be administered intravenously by a health care professional.
Patients should be instructed to read the Medication Guide carefully before ibandronate is administered and to re-read it each time the prescription is renewed because it contains important information the patient should know about ibandronate.
Inform patients that ibandronate sodium injection is administered once every 3 months. If the dose is missed, the injection should be administered as soon as it can be rescheduled. Thereafter, injections should be scheduled every 3 months from the date of the last injection. Do not administer ibandronate sodium injection more frequently than once every 3 months.
Inform patients that they should take supplemental calcium and vitamin D if their dietary intake is inadequate [see Warnings and Precautions (5.1)].
Inform patients ibandronate sodium injection should not be administered to patients with creatinine clearance less than 30 mL/min. A serum creatinine should be measured prior to each dose [see Warnings and Precautions (5.3)].
Inform patients that the most common side effects of ibandronate include arthralgia, back pain, hypertension, and abdominal pain. Flu-like symptoms (acute phase reaction) may occur within 3 days following infusion, and usually subside within 24 to 48 hours without specific therapy.
Inform patients that there have been reports of persistent pain and/or a non-healing sore of the mouth or jaw, primarily in patients treated with bisphosphonates for other illnesses. If they experience these symptoms, they should inform their physician or dentist.
Inform patients that severe bone, joint, and/or muscle pain have been reported in patients taking bisphosphonates, including ibandronate. Patients should report severe symptoms if they develop.
Inform patients that atypical femur fractures in patients on bisphosphonate therapy have been reported. Patients should report new thigh or groin pain and undergo evaluation to rule out a femoral fracture.
Distributed by:
Eugia US LLC
279 Princeton-Hightstown Rd.
E. Windsor, NJ 08520
Manufactured by:
Eugia Pharma Specialities Limited
Hyderabad - 500032
India

MEDICATION GUIDE

IBANDRONATE SODIUM
(eye ban′ droe nate soe′ dee um)
INJECTION
for intravenous use

Read the Medication Guide that comes with ibandronate sodium injection before you start taking it and each time you get a refill. There may be new information. This Medication Guide does not take the place of talking with your doctor about your medical condition or treatment. Talk to your doctor if you have any questions about ibandronate sodium injection.

What is the most important information I should know about ibandronate sodium injection?

Ibandronate sodium injection is given in your vein (intravenously) and only given by a healthcare provider. Do not give ibandronate sodium injection to yourself.

Ibandronate sodium injection can cause serious side effects including:

1. Low calcium levels in your blood (hypocalcemia)
2. Severe allergic reaction (anaphylactic reaction)
3. Severe kidney problems
4. Severe jaw bone problems (osteonecrosis)
5. Bone, joint or muscle pain
6. Unusual breaks in thigh and other bone

1. Low calcium levels in your blood (hypocalcemia).

Ibandronate sodium injection may lower the calcium levels in your blood. If you have low blood calcium before you start taking ibandronate sodium injection, it may get worse during treatment. Your low blood calcium must be treated before you receive ibandronate sodium injection. Most people with low blood calcium levels do not have symptoms, but some people may have symptoms. Call your doctor right away if you have symptoms of low blood calcium such as:

- Spasms, twitches, or cramps in your muscles
- Numbness or tingling in your fingers, toes, or around your mouth

Your doctor may prescribe calcium and vitamin D to help prevent low calcium levels in your blood, while you receive ibandronate sodium injection. Take calcium and vitamin D as your doctor tells you to.

2. Severe allergic reactions.

Some people who received ibandronate sodium injection had severe allergic reactions (anaphylactic reactions) that led to death. Get medical help right away if you have any of the symptoms of a serious allergic reaction such as:

- Swelling of your face, lips, mouth or tongue
- Trouble breathing
- Wheezing
- Severe itching
- Skin rash, redness or swelling
- Dizziness or fainting
- Fast heartbeat or pounding in your chest
- Sweating

3. Severe kidney problems.

Severe kidney problems, including kidney failure, may happen when you receive ibandronate sodium injection. Your doctor should do blood tests to check your kidneys before you receive each dose of ibandronate sodium injection.

4. Severe jaw bone problems (osteonecrosis).

Severe jaw bone problems may happen when you receive ibandronate sodium injection. Your doctor may examine your mouth before you start ibandronate sodium injection. Your doctor may tell you to see your dentist before you start ibandronate sodium injection. It is important for you to practice good mouth care during treatment with ibandronate sodium injection.

5. Bone, joint, or muscle pain.

Some people who receive ibandronate sodium injection develop severe bone, joint, or muscle pain.

6. Unusual breaks in thigh and other bones.

Some people have had unusual bone breaks, including thigh bone, when taking ibandronate sodium injection. A break in the thigh bone can feel like a new pain in your hip, groin, or thigh. People taking ibandronate sodium injection can also have breaks in other bones.

Call your doctor right away if you have any of these side effects.

What is ibandronate sodium injection?

Ibandronate sodium injection is a prescription medicine used to treat osteoporosis in women after menopause. Ibandronate sodium injection helps increase bone mass and helps reduce the chance of having a spinal fracture (break).

It is not known how long ibandronate sodium injection works for the treatment of osteoporosis. You should see your doctor regularly to determine if ibandronate sodium injection is still right for you.

It is not known if ibandronate sodium injection is safe and effective in children.

Who should not receive ibandronate sodium injection?

Do not receive ibandronate sodium injection if you:

- Have low levels of calcium in your blood
- Are allergic to ibandronate sodium or any of the ingredients in ibandronate sodium injection. See the end of this leaflet for a complete list of ingredients in ibandronate sodium injection.

What should I tell my healthcare provider before receiving ibandronate sodium injection?

Before you receive ibandronate sodium injection, tell your doctor if you:

- Have low blood calcium
- Plan to have dental surgery or teeth removed
- Have kidney problems or other problems that may affect your kidneys
- Have been told you have trouble absorbing minerals in your stomach or intestines (malabsorption syndrome)
- Are pregnant or plan to become pregnant. It is not known if ibandronate sodium injection can harm your unborn baby.
- Are breast-feeding or plan to breast-feed. It is not known if ibandronate passes into your milk and may harm your baby.

Tell your doctor and dentist about all the medicines you take, including prescription and non-prescription medicines, vitamins and herbal supplements.

Know the medicines you take. Keep a list of them and show it to your healthcare provider and pharmacist each time you get a new medicine.

How should I receive ibandronate sodium injection?

- Ibandronate sodium injection is given 1 time every 3 months by a healthcare provider.
- If you miss a dose of ibandronate sodium injection, call your doctor or healthcare provider to schedule your next dose.

What are the possible side effects of ibandronate sodium injection?

Ibandronate sodium injection may cause serious side effects.

- See “What is the most important information I should know about ibandronate sodium injection?”

The most common side effects of ibandronate sodium injection include:

- Pain in your bones, joints or muscles
- Back pain
- Abdominal pain
- Flu-like symptoms may happen within 3 days after you receive ibandronate sodium injection. Symptoms include:
- fever
- chills
- bone, joint, or muscle pain
- fatigue

If you have flu-like symptoms, they should get better within 24 to 48 hours.

Some people have pain or a sore that will not heal in their mouth or jaw while they receive ibandronate sodium injection. Tell your doctor or dentist if you have mouth or jaw problems.

Tell your doctor if you have any side effect that bothers you or that does not go away.

These are not all the possible side effects of ibandronate sodium injection. For more information, ask your doctor or pharmacist.

Call your doctor for medical advice about side effects. You may report side effects to FDA at 1-800-FDA-1088. You may also report side effects to Eugia US LLC at 1-866-850-2876.
How should I store ibandronate sodium injection if I need to pick it up from a pharmacy?

- Store ibandronate sodium injection at room temperature between 68°F and 77°F (20°C and 25°C).

Keep ibandronate sodium injection and all medicines out of the reach of children.

General information about the safe and effective use of ibandronate sodium injection.

Medicines are sometimes prescribed for purposes other than those listed in a Medication Guide. Do not use ibandronate sodium injection for a condition for which it was not prescribed. Do not give ibandronate sodium injection to other people, even if they have the same symptoms you have. It may harm them.

This Medication Guide summarizes the most important information about ibandronate sodium injection. If you would like more information, talk with your doctor. You can ask your doctor or pharmacist for information about ibandronate sodium injection that is written for health professionals.

What are the ingredients in ibandronate sodium injection?

Active ingredient: ibandronate sodium

Inactive ingredients: glacial acetic acid, sodium acetate trihydrate, sodium chloride and water
This Medication Guide has been approved by the U.S. Food and Drug Administration.

Distributed by:
Eugia US LLC
279 Princeton-Hightstown Rd.
E. Windsor, NJ 08520
Manufactured by:
Eugia Pharma Specialities Limited
Hyderabad - 500032
India
Revised: January 2026

TERUMO® Surflo® Safety Winged Infusion Set —

Instructions for Use: IV Administration

Aseptic technique, proper skin preparation and continued protection of the site are essential. Observe Universal Precautions on all patients.

Caution: Keep hands behind the needle at all times during use and disposal.

Instructions for Device Assembly

1. Open the package.
2. Remove the rubber cap from the tip of the syringe containing the ibandronate sodium injection and the protective SV cap from hub at the end of the tubing opposite the butterfly needle.
3. Insert the tip of the syringe into the hub and twist as firm pressure is applied to assure a tight connection.
4. Proceed with priming and confirm that administration fluid comes from the needle.

Venipuncture and Administration

1. Flip the safety shield back away from the needle towards the tubing. Grasp wings securely.
2. Remove the needle protector. Caution: Care should be taken not to touch the needle.
3. Perform venipuncture and confirm proper positioning of the needle in the vein.
4. Carefully allow wings to return to starting position and conform to the shape of the skin.
5. Further secure the position of the winged infusion set per facility protocol.

After Use

1. Remove tape, if present, from wings.
2. Flip the safety shield forward toward the needle. Grasp a wing and the safety shield between your thumb and index finger. Completely remove the needle from the puncture site and apply digital pressure to the site using a sterile gauze pad held in the opposite hand (Fig. 1).
3. With the wing and shield between your thumb and index finger pinch together (or press the safety shield against a hard surface such as a bedside table) until an audible click is heard (Fig. 2).
4. Visually confirm activation of the safety feature (Fig. 3).
5. Dispose of used needles and materials following the policies and procedures of your facility, as well as federal and local regulations for “Sharps Disposal.”

®Registered Trademark. Surflo is a registered trademark of TERUMO CORPORATION.

PACKAGE LABEL-PRINCIPAL DISPLAY PANEL - 3 mg per 3 mL (1 mg/mL) - Prefilled Syringe Label

Rx only NDC 55150-191-83
Ibandronate Sodium
Injection
3 mg per 3 mL
(1 mg/mL)
Sterile. For Intravenous Use Only.
Mfd. in India for:
Eugia US LLC, E. Windsor, NJ 08520
P1433245 Code: TS/DRUGS/13/2010

PACKAGE LABEL-PRINCIPAL DISPLAY PANEL - 3 mg per 3 mL (1 mg/mL) - Prefilled Syringe Blister Label

Rx only NDC 55150-191-83
Ibandronate Sodium
Injection
3 mg per 3 mL
(1 mg/mL)*
PHARMACIST: Dispense the enclosed Medication Guide to each
patient.
Sterile. For Intravenous Use Only. Single-Dose Prefilled Syringe,
Discard unused portion. Ibandronate Sodium Injection
3 mg per 3 mL (1 mg/mL)
eugia

PACKAGE LABEL-PRINCIPAL DISPLAY PANEL - 3 mg per 3 mL (1 mg/mL) - Prefilled Syringe-Carton

Rx only NDC 55150-191-83
Ibandronate Sodium
Injection
3 mg per 3 mL
(1 mg/mL)*
PHARMACIST: Dispense the enclosed Each Carton Contains:
Medication Guide to each patient. 1 Single-Dose Prefilled Syringe,
1 Needle
Sterile. For Intravenous Use Only. Discard unused portion.
eugia